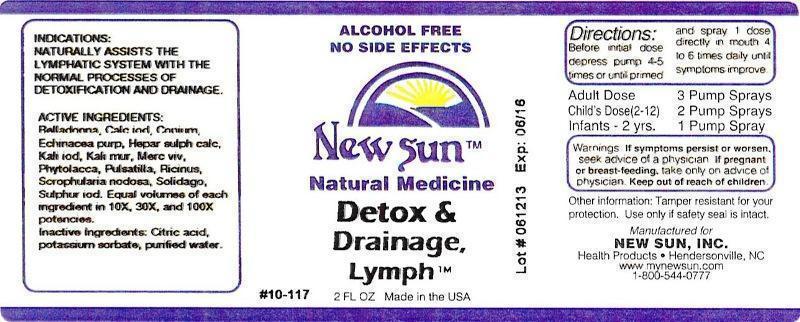 DRUG LABEL: Detox and Drainage, Lymph
NDC: 66579-0058 | Form: LIQUID
Manufacturer: New Sun Inc.
Category: homeopathic | Type: HUMAN OTC DRUG LABEL
Date: 20140905

ACTIVE INGREDIENTS: ATROPA BELLADONNA 10 [hp_X]/59 mL; CALCIUM IODIDE 10 [hp_X]/59 mL; CONIUM MACULATUM FLOWERING TOP 10 [hp_X]/59 mL; ECHINACEA PURPUREA 10 [hp_X]/59 mL; CALCIUM SULFIDE 10 [hp_X]/59 mL; POTASSIUM IODIDE 10 [hp_X]/59 mL; POTASSIUM CHLORIDE 10 [hp_X]/59 mL; MERCURY 10 [hp_X]/59 mL; PHYTOLACCA AMERICANA ROOT 10 [hp_X]/59 mL; PULSATILLA VULGARIS 10 [hp_X]/59 mL; RICINUS COMMUNIS SEED 10 [hp_X]/59 mL; SCROPHULARIA NODOSA 10 [hp_X]/59 mL; SOLIDAGO VIRGAUREA FLOWERING TOP 10 [hp_X]/59 mL; SULFUR IODIDE 10 [hp_X]/59 mL
INACTIVE INGREDIENTS: CITRIC ACID MONOHYDRATE; POTASSIUM SORBATE; WATER

Detox and Drainage, Lymph

DOSAGE AND ADMINISTRATION

Directions: Before initial dose depress pump 4-5 times or until primed and spray 1 dose directly in mouth 4 to 6 times daily until symptoms improve.

Adult Dose: 3 Pump Sprays

Child's Dose (2-12): 2 Pump Sprays

Infants - 2 yrs: 1 Pump Spray

WARNINGS

Warnings: If symptoms persist or worsen, seek advice of a physician. If pregnant or breast-feeding, take only on advice of physician.

Keep out of reach of children.

Other information: Tamper resistant for your protection. Use only if safety seal is intact.

PURPOSE

Indications: Naturally assists the lymphatic system with the normal processes of detoxification and drainage.

ACTIVE INGREDIENT

Active Ingredients: Belladonna, Calcarea iodata, Conium maculatum, Echinacea purpurea, Hepar sulphuris calcareum, Kali iodatum, Kali muriaticum, Mercurius vivus, Phytolacca decandra, Pulsatilla, Ricinus communis, Scrophularia nodosa, Solidago virgaurea, Sulphur iodatum. Equal volumes of each ingredient in 10X, 30X, and 100X potencies.

Inactive Ingredient: Citric acid, potassium sorbate, purified water.

INDICATIONS AND USAGE

Indications: Naturally assists the lymphatic system with the normal processes of detoxification and drainage.